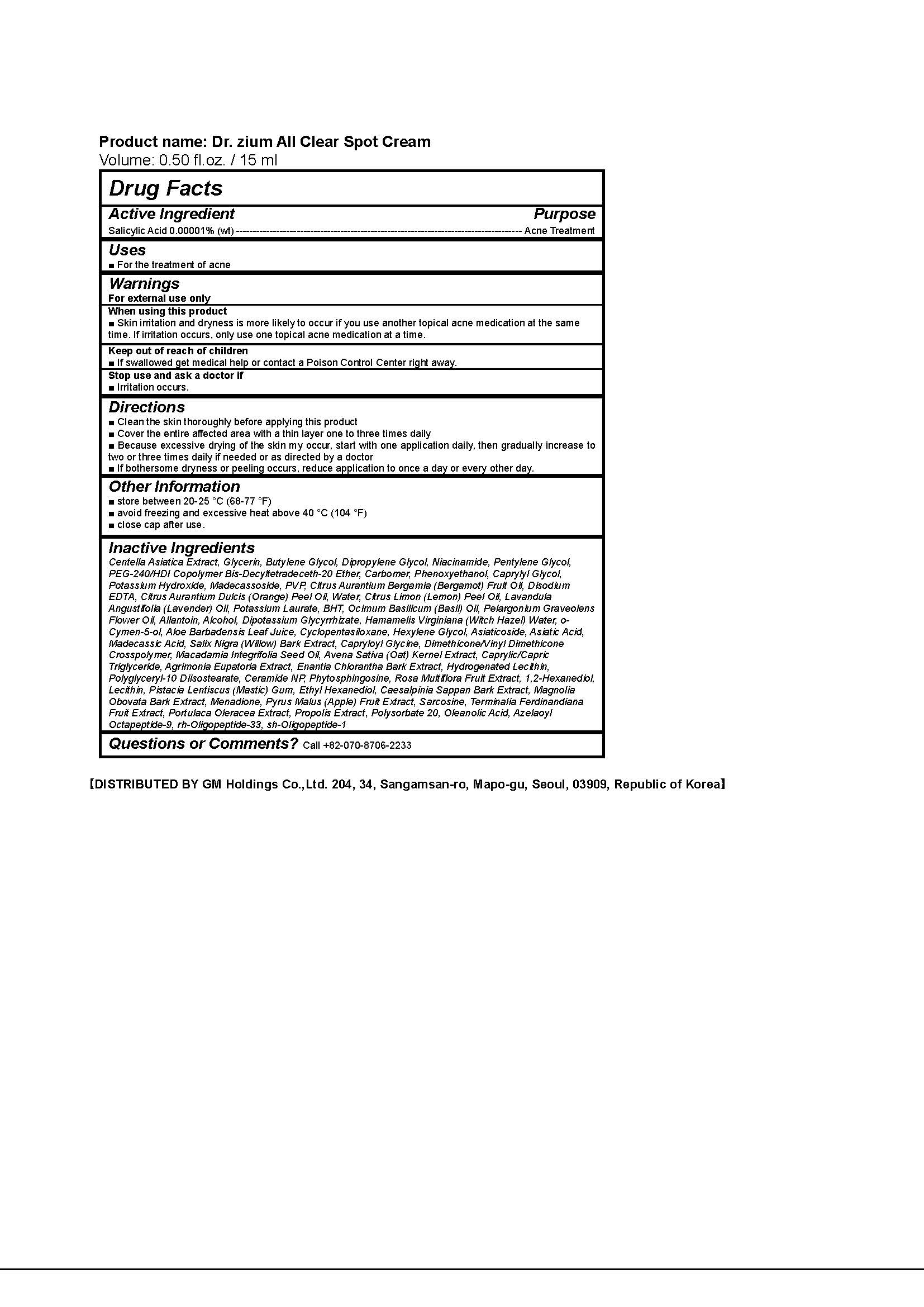 DRUG LABEL: Dr.zium All Clear Spot
NDC: 69278-001 | Form: CREAM
Manufacturer: GM Holdings Co., Ltd
Category: otc | Type: HUMAN OTC DRUG LABEL
Date: 20180122

ACTIVE INGREDIENTS: SALICYLIC ACID 0.00001 g/100 mL
INACTIVE INGREDIENTS: KAKADU PLUM; WATER; NIACINAMIDE

ACTIVE INGREDIENT

Salicylic Acid

INACTIVE INGREDIENT

Niacinamide, Terminalia Ferdinandiana Fruit Extract, Aazelaoyl Octapeptide-9, Water, etc

PURPOSE

Acne Treatment

keep out of reach of the children

INDICATIONS AND USAGE

Apply an adequate amount to the trouble area and absorb with gentle dabbing

Warnings

Do not use if you have very sensitive skin or are sensitive to Salicylic Acid

Ask a doctor or pharmacist before use if you are using other topical acne medications at the same time or immediately following use of this product. This may increase dryness or irritation of the skin. If this occurs, only one medication should be used unless directed by a doctor.

Keep out of reach of children. If swallowed, get medical help or contact a Poison Control Center right away.

DOSAGE AND ADMINISTRATION

For external use only